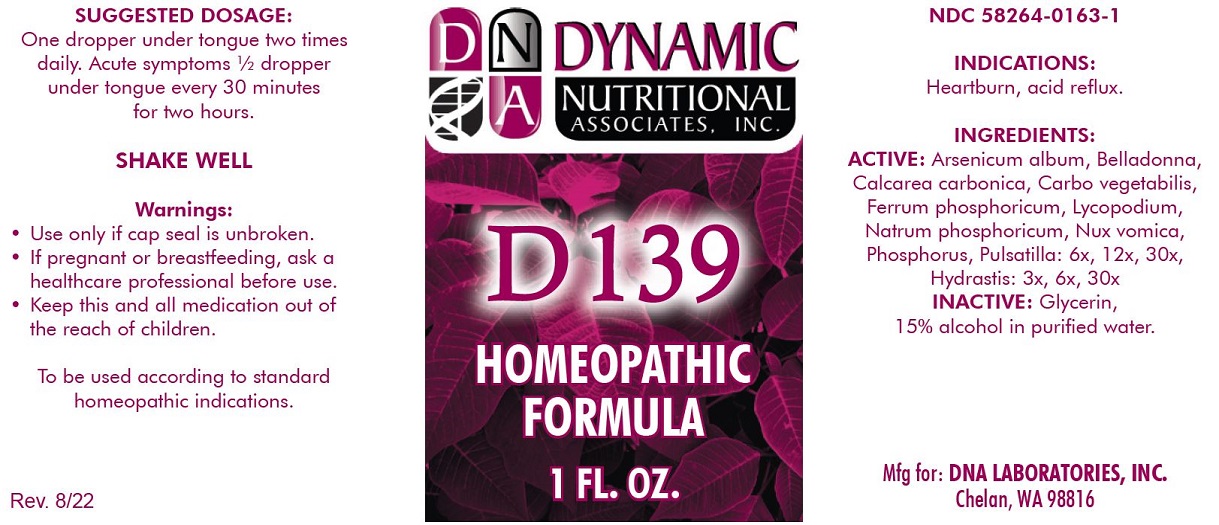 DRUG LABEL: D-139
NDC: 58264-0163 | Form: SOLUTION
Manufacturer: DNA Labs, Inc.
Category: homeopathic | Type: HUMAN OTC DRUG LABEL
Date: 20250113

ACTIVE INGREDIENTS: ANEMONE PRATENSIS 6 [hp_X]/1 mL; LYCOPODIUM CLAVATUM SPORE 6 [hp_X]/1 mL; PHOSPHORUS 6 [hp_X]/1 mL; FERROSOFERRIC PHOSPHATE 6 [hp_X]/1 mL; ARSENIC TRIIODIDE 6 [hp_X]/1 mL; ATROPA BELLADONNA 6 [hp_X]/1 mL; SODIUM PHOSPHATE, DIBASIC, HEPTAHYDRATE 6 [hp_X]/1 mL; ACTIVATED CHARCOAL 6 [hp_X]/1 mL; OYSTER SHELL CALCIUM CARBONATE, CRUDE 6 [hp_X]/1 mL; GOLDENSEAL 3 [hp_X]/1 mL; STRYCHNOS NUX-VOMICA SEED 6 [hp_X]/1 mL
INACTIVE INGREDIENTS: ALCOHOL; WATER

D-139

NDC 58264-0163-1

INDICATIONS

PURPOSE

Heartburn, acid reflux.

INGREDIENTS

ACTIVE

Arsenicum album 6x, Belladonna 6x, Calcarea carbonica 6x, Carbo vegetabilis 6x, Ferrum phosphoricum 6x, Lycopodium 6x, Natrum phosphoricum 6x, Nux vomica 6x, Phosphorus 6x, Pulsatilla 6x, Hydratsis 3x

INACTIVE

20% alcohol in purified water.

SUGGESTED DOSAGE

One dropper under tongue two times daily. Acute symptoms 1/2 dropper under tongue every 30 minutes for two hours.

STORAGE AND HANDLING

SHAKE WELL

Warnings

- Use only if cap seal is unbroken

PREGNANCY OR BREAST FEEDING

- If pregnant or breastfeeding, ask a healthcare professional before use.

KEEP OUT OF REACH OF CHILDREN

- Keep this and all medication out of the reach of children.

To be used according to standard homeopathic indications.

PRINCIPAL DISPLAY PANEL - 1 FL. OZ. Bottle Label

DYNAMIC

NUTRITIONAL

ASSOCIATES, INC.

D-139

HOMEOPATHIC

STRESS FORMULA

1 FL. OZ.